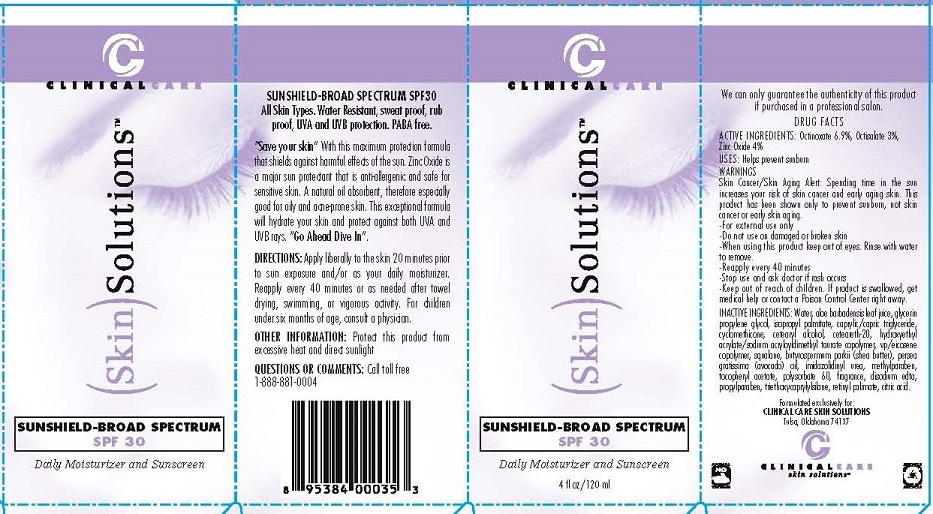 DRUG LABEL: SUNSHIELD


NDC: 70900-202 | Form: CREAM
Manufacturer: CLINICAL CARE SKIN SOLUTIONS, INC
Category: otc | Type: HUMAN OTC DRUG LABEL
Date: 20230221

ACTIVE INGREDIENTS: OCTINOXATE 6.9 g/100 mL; OCTISALATE 3 g/100 mL; ZINC OXIDE 4 g/100 mL
INACTIVE INGREDIENTS: WATER; ALOE VERA LEAF; GLYCERIN; PROPYLENE GLYCOL; ISOPROPYL PALMITATE; MEDIUM-CHAIN TRIGLYCERIDES; CYCLOMETHICONE; CETOSTEARYL ALCOHOL; POLYOXYL 20 CETOSTEARYL ETHER; VINYLPYRROLIDONE/EICOSENE COPOLYMER; HYDROXYETHYL ACRYLATE/SODIUM ACRYLOYLDIMETHYL TAURATE COPOLYMER (45000 MPA.S AT 1%); SQUALANE; SHEA BUTTER; AVOCADO OIL; IMIDUREA; METHYLPARABEN; .ALPHA.-TOCOPHEROL ACETATE; POLYSORBATE 60; EDETATE DISODIUM; PROPYLPARABEN; TRIETHOXYCAPRYLYLSILANE; VITAMIN A PALMITATE; CITRIC ACID MONOHYDRATE

CLINICAL CARE SKIN SOLUTIONS - SUNSHIELD (70900-202)

ACTIVE INGREDIENTS:

OCTINOXATE 6.9%, OCTISALATE 3%, ZINC OXIDE 4%

USES:

HELPS PREVEN SUNBURN

WARNINGS:

SKIN CANCER/SKIN AGING ALERT: SPENDING TIME IN THE SUN INCREASES YOUR RISK OF SKIN CANCER AND EARLY AGING SKIN. THIS PRODUCT HAS BEEN SLOWN ONLY TO PREVEN SUNBURN, NOT SKIN CANCER OR EALY SKIN AGING.

- FOR EXTERNAL USE ONLY.
- DO NOT USE ON DAMAGED OR BROKEN SKIN.
- WHEN USING THIS PRODUCT KEEP OUT OF EYES. RINSE WITH WATER TO REMOVE.
- REAPPLY EVERY 40 MINUTES.
- STOP USE AND ASK DOCTOR IF RASH OCCURS.

KEEP OUT OF REACH OF CHILDREN.

IF PRODUCT IS SWALLOWED, GET MEDICAL HELP OR CONTACT A POISON CONTROL CENTER RIGHT AWAY.

INACTIVE INGREDIENTS:

WATER, ALOE BARBADENSIS LEAF JUICE, GLYCERIN, PROPYLENE GLYCOL, ISOPROPYL PALMITATE, CAPRYLIC/CAPRIC TRIGLYCERIDE, CYCLOMETHICONE, CETEARYL ALCOHOL, CETEARETH-2, HYDROXYETHYL ACRYLATE/SODIUM ACRYLOYLDIMETHYL TAURATE COPOLYMER, VP/EICOSENE COPOLYMER, SQUALANE, BUTYROSPERMUM PARKII (SHEA) BUTTER, PERSEA GRATISSIMA (AVOCADO) OIL, IMIDAZOLIDINYL UREA, METHYLPARABEN, TOCOPHERYL ACETATE, POLYSORBATE 60, FRAGRANCE, DISODIUM EDTA, PROPYLPARABEN, TRIETHOXYCAPRYLYLSYLANE, RETINYL PALMITATE, CITRIC ACID.